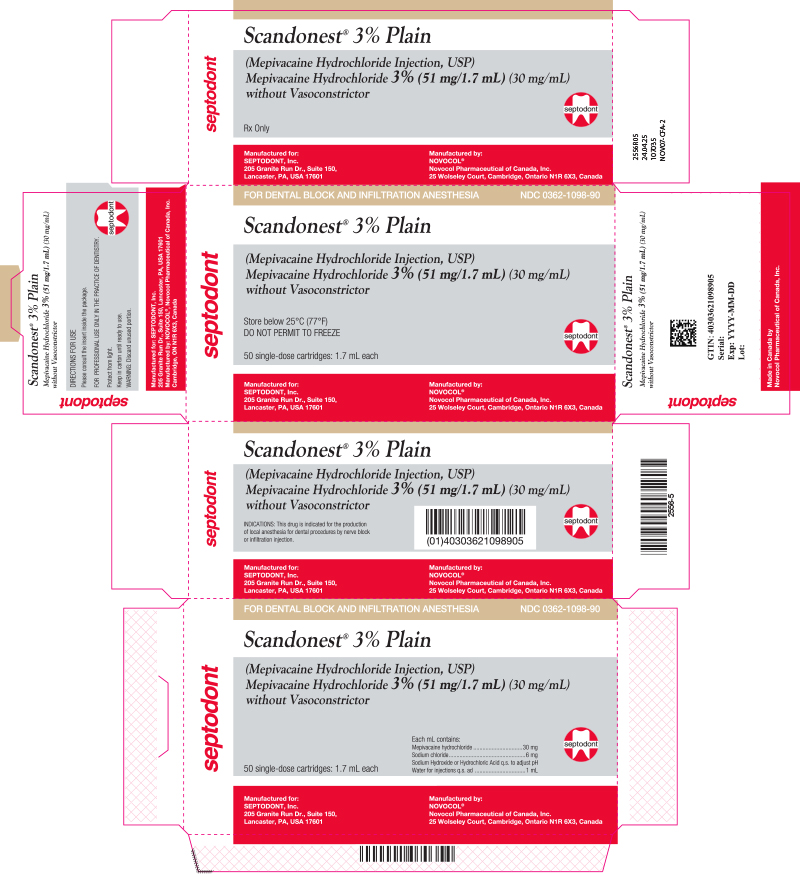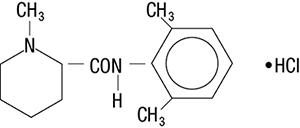 DRUG LABEL: Scandonest 3% Plain
NDC: 0362-1098 | Form: injection, solution
Manufacturer: Septodont, Inc.
Category: prescription | Type: HUMAN PRESCRIPTION DRUG LABEL
Date: 20250529

ACTIVE INGREDIENTS: Mepivacaine Hydrochloride 30 mg/1 mL
INACTIVE INGREDIENTS: Sodium Chloride 6 mg/1 mL; SODIUM HYDROXIDE; Water

Scandonest® 3% Plain
(Mepivacaine Hydrochloride Injection, USP)
Mepivacaine Hydrochloride 3% (51 mg/1.7mL) (30 mg/mL) without Vasoconstrictor

Rx Only

THIS SOLUTION IS INTENDED FOR DENTAL USE ONLY.

DESCRIPTION:

Mepivacaine Hydrochloride, a tertiary amine used as a local anesthetic, is 1-methyl-2', 6' - pipecoloxylidide monohydrochloride with the following structural formula:

C15H22N2O • HCI M.W. 282.81

It is a white, crystalline, odorless powder soluble in water, but very resistant to both acid and alkaline hydrolysis.

DENTAL CARTRIDGES MAY NOT BE AUTOCLAVED.
SCANDONEST® 3% Plain (mepivacaine hydrochloride injection 3% (51 mg/1.7 mL) (30 mg/mL)) is a sterile solution for injection.

COMPOSITION:

 | CARTRIDGE
Each mL contains: | 3%
Mepivacaine Hydrochloride | 30 mg
Sodium Chloride | 6 mg
Sodium Hydroxide or Hydrochloric Acid q.s. to adjust pH
Water For Injection, qs. ad. | 1 mL
The pH of the 3% cartridge solution is adjusted between 4.5 and 6.8 with NaOH.

CLINICAL PHARMACOLOGY:

SCANDONEST® stabilizes the neuronal membrane and prevents the initiation and transmission of nerve impulses, thereby effecting local anesthesia.

SCANDONEST® is rapidly metabolized, with only a small percentage of the anesthetic (5 to 10 percent) being excreted unchanged in the urine. SCANDONEST® because of its amide structure, is not detoxified by the circulating plasma esterases. The liver is the principal site of metabolism, with over 50 percent of the administered dose being excreted into the bile as metabolites. Most of the metabolized mepivacaine is probably resorbed in the intestine and then excreted into the urine since only a small percentage is found in the feces. The principal route of excretion is via the kidney. Most of the anesthetic and its metabolites are eliminated within 30 hours. It has been shown that hydroxylation and N-demethylation, which are detoxification reactions, play important roles in the metabolism of the anesthetic. Three metabolites of mepivacaine have been identified from adult humans: two phenols, which are excreted almost exclusively as their glucuronide conjugates, and the N-demethylated compound (2’, 6’- pipecoloxylidide).

The onset of action is rapid (30 to 120 seconds in the upper jaw; 1 to 4 minutes in the lower jaw) and SCANDONEST® 3% Plain will ordinarily provide operating anesthesia of 20 minutes in the upper jaw and 40 minutes in the lower jaw.

SCANDONEST® does not ordinarily produce irritation or tissue damage.

INDICATIONS AND USAGE:

Mepivacaine is indicated for production of local anesthesia for dental procedures by infiltration or nerve block in adults and pediatric patients.

CONTRAINDICATIONS:

SCANDONEST® is contraindicated in patients with a known hypersensitivity to amide-type local anesthetics.

WARNINGS:

RESUSCITATIVE EQUIPMENT AND DRUGS SHOULD BE IMMEDIATELY AVAILABLE. (See ADVERSE REACTIONS).

Reactions resulting in fatality have occurred on rare occasions with the use of local anesthetics, even in the absence of a history of hypersensitivity.

Fatalities may occur with use of local anesthetics in the head and neck region as the result of retrograde arterial flow to vital CNS areas even when maximum recommended doses are observed. The practitioner should be alert to early evidences of alteration in sensorium or vital signs.

SCANDONEST® 3% Plain is SULFITE FREE.

Methemoglobinemia: Cases of methemoglobinemia have been reported in association with local anesthetic use; SCANDONEST®, along with other local anesthetics, is capable of producing this condition. Although all patients are at risk for methemoglobinemia, patients with glucose-6-phosphate dehydrogenase deficiency, congenital or idiopathic methemoglobinemia, cardiac or pulmonary compromise, infants under 6 months of age, and concurrent exposure to oxidizing agents or their metabolites are more susceptible to developing clinical manifestations of the condition. If local anesthetics must be used in these patients, close monitoring for symptoms and signs of methemoglobinemia is recommended.

Signs of methemoglobinemia may occur immediately or may be delayed some hours after exposure, and are characterized by cyanosis of the skin, nail beds and lips, and/or abnormal coloration of the blood, fatigue and weakness. Methemoglobin levels may continue to rise; therefore, immediate treatment is required to avert more serious central nervous system and cardiovascular adverse effects, including seizures, coma, arrhythmias, and death. Discontinue SCANDONEST® and any other oxidizing agents. Depending on the severity of the signs and symptoms, patients may respond to supportive care, i.e., oxygen therapy, hydration. If methemoglobinemia does not respond to administration of oxygen, a more severe clinical presentation may require treatment with methylene blue, exchange transfusion, or hyperbaric oxygen.

PRECAUTIONS:

The safety and effectiveness of mepivacaine depend upon proper dosage, correct technique, adequate precautions, and readiness for emergencies.

The lowest dose that results in effective anesthesia should be used to avoid high plasma levels and possible adverse effects. Injection of repeated doses of mepivacaine may cause significant increase in blood levels with each repeated dose due to slow accumulation of the drug or its metabolites, or due to slower metabolic degradation than normal.

Tolerance varies with the status of the patient. Debilitated, elderly patients, acutely ill patients, and children should be given reduced doses commensurate with their weight and physical status. Mepivacaine should be used with caution in patients with a history of severe disturbances of cardiac rhythm or heart block.

INJECTIONS SHOULD ALWAYS BE MADE SLOWLY WITH ASPIRATION TO AVOID INTRAVASCULAR INJECTION AND THEREFORE SYSTEMIC REACTION.

If sedatives are employed to reduce patient apprehension, use reduced doses, since local anesthetic agents, like sedatives, are central nervous system depressants which in combination may have an additive effect. Young children should be given minimal doses of each agent.

Changes in sensorium such as excitation, disorientation or drowsiness may be early indications of a high blood level of the drug and may occur following inadvertent intravascular administration or rapid absorption of mepivacaine.

Local anesthetic procedures should be used with caution when there is inflammation and/or sepsis in the region of the proposed injection.

Information for Patients/Patient Counseling Information:

The patient should be cautioned against loss of sensation and possibility of biting trauma should the patient attempt to eat or chew gum prior to return of sensation. Inform patients that use of local anesthetics may cause methemoglobinemia, a serious condition that must be treated promptly. Advise patients or caregivers to seek immediate medical attention if they or someone in their care experience the following signs or symptoms: pale, gray, or blue colored skin (cyanosis); headache; rapid heart rate; shortness of breath; lightheadedness; or fatigue.

Clinically Significant Drug Interactions:

Patients who are administered local anesthetics are at increased risk of developing methemoglobinemia when concurrently exposed to the following drugs, which could include other local anesthetics:

EXAMPLES OF DRUGS ASSOCIATED WITH METHEMOGLOBINEMIA:
Class | Examples
Nitrates/Nitrites | nitric oxide, nitroglycerin, nitroprusside, nitrous oxide
Local anesthetics | articaine, benzocaine, bupivacaine, lidocaine, mepivacaine, prilocaine, procaine, ropivacaine, tetracaine
Antineoplastic Agents | cyclophosphamide, flutamide, hydroxyurea, ifosfamide, rasburicase
Antibiotics | dapsone, nitrofurantoin, para-aminosalicylic acid, sulfonamides
Antimalarials | chloroquine, primaquine
Anticonvulsants | phenobarbital, phenytoin, sodium valproate
Other drugs | acetaminophen, metoclopramide, quinine, sulfasalazine

MEPIVACAINE SHOULD BE USED WITH CAUTION IN PATIENTS WITH KNOWN DRUG ALLERGIES AND SENSITIVITIES. A thorough history of the patient’s prior experience with mepivacaine or other local anesthetics as well as concomitant or recent drug use should be taken (see CONTRAINDICATIONS). Patients allergic to methylparaben or para-aminobenzoic acid derivatives (procaine, tetracaine, benzocaine, etc.) have not shown cross-sensitivity to agents of the amide type such as mepivacaine. Since mepivacaine is metabolized in the liver and excreted by the kidneys, it should be used cautiously in patients with liver and renal disease.

Carcinogenesis, Mutagenesis, Impairment of Fertility:

Studies of mepivacaine HCl in animals to evaluate the carcinogenic and mutagenic potential or the effect on fertility have not been conducted.

Pregnancy: Teratogenic Effects: Pregnancy Category C:

Animal reproduction studies have not been conducted with this solution. It is also not known whether this solution can cause fetal harm when administered to a pregnant woman or can affect reproductive capacity. This solution should be given to a pregnant woman only if clearly needed.

Nursing Mothers:

It is not known whether this drug is excreted in human milk. Because many drugs are excreted in human milk, caution should be exercised when this solution is administered to a nursing woman.

Pediatric Use:

Great care must be exercised in adhering to safe concentrations and dosages for pedodontic administration (see DOSAGE AND ADMINISTRATION).

ADVERSE REACTIONS:

Reactions to SCANDONEST® are characteristic of those associated with other amide-type local anesthetics. Systemic adverse reactions involving the central nervous system and the cardiovascular system usually result from high plasma levels (which may be due to excessive dosage, rapid absorption, inadvertent intravascular injection, or slow metabolic degradation), injection technique, or volume of injection.

A small number of reactions may result from hypersensitivity, idiosyncrasy or diminished tolerance to normal dosage on the part of the patient.

Persistent paresthesias of the lips, tongue, and oral tissues have been reported with the use of mepivacaine, with slow, incomplete, or no recovery. These post-marketing events have been reported chiefly following nerve blocks in the mandible and have involved the trigeminal nerve and its branches.

Reactions involving the central nervous system are characterized by excitation and/or depression. Nervousness, dizziness, blurred vision, or tremors may occur followed by drowsiness, convulsions, unconsciousness, and possible respiratory arrest. Since excitement may be transient or absent, the first manifestations may be drowsiness merging into unconsciousness and respiratory arrest.

Cardiovascular reactions are depressant. They may be the result of direct drug effect or more commonly in dental practice, the result of vasovagal reaction, particularly if the patient is in the sitting position. Failure to recognize premonitory signs such as sweating, feeling of faintness, changes in pulse or sensorium may result in progressive cerebral hypoxia and seizure or serious cardiovascular catastrophe. Management consists of placing the patient in the recumbent position and administration of oxygen. Vasoactive drugs such as Ephedrine or Methoxamine may be administered intravenously.

Allergic reactions are rare and may occur as a result of sensitivity to the local anesthetic and are characterized by cutaneous lesions of delayed onset or urticaria, edema and other manifestations of allergy. The detection of sensitivity by skin testing is of limited value. As with other local anesthetics, anaphylactoid reactions to mepivacaine have occurred rarely. The reaction may be abrupt and severe and is not usually dose related. Localized puffiness and swelling may occur0

OVERDOSAGE:

Treatment of a patient with toxic manifestations consists of assuring and maintaining a patent airway and supporting ventilation (respiration) as required. This usually will be sufficient in the management of most reactions.

Should a convulsion persist despite ventilatory therapy, small increments of anticonvulsive agents may be given intravenously, such as benzodiazepine (e.g., diazepam) or ultrashort-acting barbiturates (e.g., thiopental or thiamylal) or short-acting barbiturates (e.g., pentobarbital or secobarbital). Cardiovascular depression may require circulatory assistance with intravenous fluids and/or vasopressor (e.g., Ephedrine) as dictated by the clinical situation. Allergic reactions should be managed by conventional means.

Intravenous and subcutaneous LD50’s in mice for mepivacaine hydrochloride 3% are 33 and 258 mg/kg, respectively.

DOSAGE AND ADMINISTRATION:

As with all local anesthetics, the dose varies and depends upon the area to be anesthetized, the vascularity of the tissues, individual tolerance and the technique of anesthesia. The lowest dose needed to provide effective anesthesia should be administered. For specific techniques and procedures refer to standard dental manuals and textbooks.

For infiltration and block injections in the upper or lower jaw, the average dose of 1 cartridge will usually suffice. Each cartridge contains 1.7 mL (51 mg of mepivacaine).

270 mg of mepivacaine (5.3 cartridges of Scandonest 3%) is usually adequate to effect anesthesia of the entire oral cavity. Whenever a larger dose seems to be necessary for an extensive procedure, the maximum dose should be calculated according to the patient’s weight. A dose of up to 3 mg per pound of body weight may be administered. At any single dental sitting the total dose for all injected sites should not exceed 400 mg in adults.

The maximum pediatric dose should be carefully calculated. Maximum dose for pediatric population =

Child’s Weight (lbs.) X Maximum Recommended Dose
150 for Adults (400 mg)

The following table, approximating these calculations, may also be used as a guide. This table is based upon a recommended maximum for larger pediatric population of 5.3 cartridges (the maximum recommended adult dose) during any single dental sitting, regardless of the pediatric patient’s weight or calculated maximum amount of drug:

Maximum Allowable Dosage*
3% Mepivacaine
Plain
3 mg/lb
(270 mg max.)
Weight
(lb) | mg | Number of Cartridges
20 | 60 | 1.2
30 | 90 | 1.8
40 | 120 | 2.3
50 | 150 | 2.9
60 | 180 | 3.5
80 | 240 | 4.7
100 | 270 | 5.3
120 | 270 | 5.3

*Adapted from Malamed, Stanley F: Handbook of medical emergencies in the dental office, ed. 2, St. Louis, 1982. The C.V. Mosby Co.

When using SCANDONEST® for infiltration or regional block anesthesia, injection should always be made slowly and with frequent aspiration. Any unused portion of a cartridge should be discarded.

Parenteral drug products should be inspected visually for particulate matter and discoloration prior to administration, whenever solution and container permit.

DISINFECTION OF CARTRIDGES:

As in the case of any cartridge, the diaphragm should be disinfected before needle puncture. The diaphragm should be thoroughly swabbed with either pure 91% isopropyl alcohol or 70% ethyl alcohol, USP, just prior to use. Many commercially available alcohol solutions contain ingredients which are injurious to container components, and therefore, should not be used. Cartridges should not be immersed in any solution.

HOW SUPPLIED:

SCANDONEST® 3% Plain; (Mepivacaine Hydrocholoride Injection USP) (NDC 0362-1098-90) is available in cardboard boxes containing 5 blisters of 10 x 1.7 mL single-dose dental cartridges, 50 per carton.

STORAGE AND HANDLING

Solution should be stored at controlled room temperature, below 25°C (77°F). Protect from light. Do not permit to freeze.

BOXES: For protection from light, retain in box until time of use. Once opened, the box should be reclosed by closing the top flap. Cartridge warmers should not be used with SCANDONEST® product.

Manufactured for SEPTODONT, Inc.,
205 Granite Run Dr., Suite 150, Lancaster, PA, USA 17601

by Novocol® Pharmaceutical of Canada Inc.,
25 Wolseley Court, Cambridge, Ontario, Canada N1R 6X3

Rev. 04/2025 (2558-10)

PRINCIPAL DISPLAY PANEL - 1.7 mL Cartridge Carton

FOR DENTAL BLOCK AND INFILTRATION ANESTHESIA NDC 0362-1098-90

Scandonest® 3% Plain

(Mepivacaine Hydrochloride Injection, USP)
Mepivacaine Hydrochloride 3% (51 mg/1.7 mL) (30mg/mL)
without Vasoconstrictor

Store below 25°C (77°F)
DO NOT PERMIT TO FREEZE

50 single-dose cartridges: 1.7 mL each

Manufactured for:
SEPTODONT, Inc.
205 Granite Run Dr., Suite 150,
Lancaster, PA, USA 17601

Manufactured by:
NOVOCOL®
Novocol Pharmaceutical of Canada, Inc.
25 Wolseley Court, Cambridge, Ontario N1R 6X3, Canada